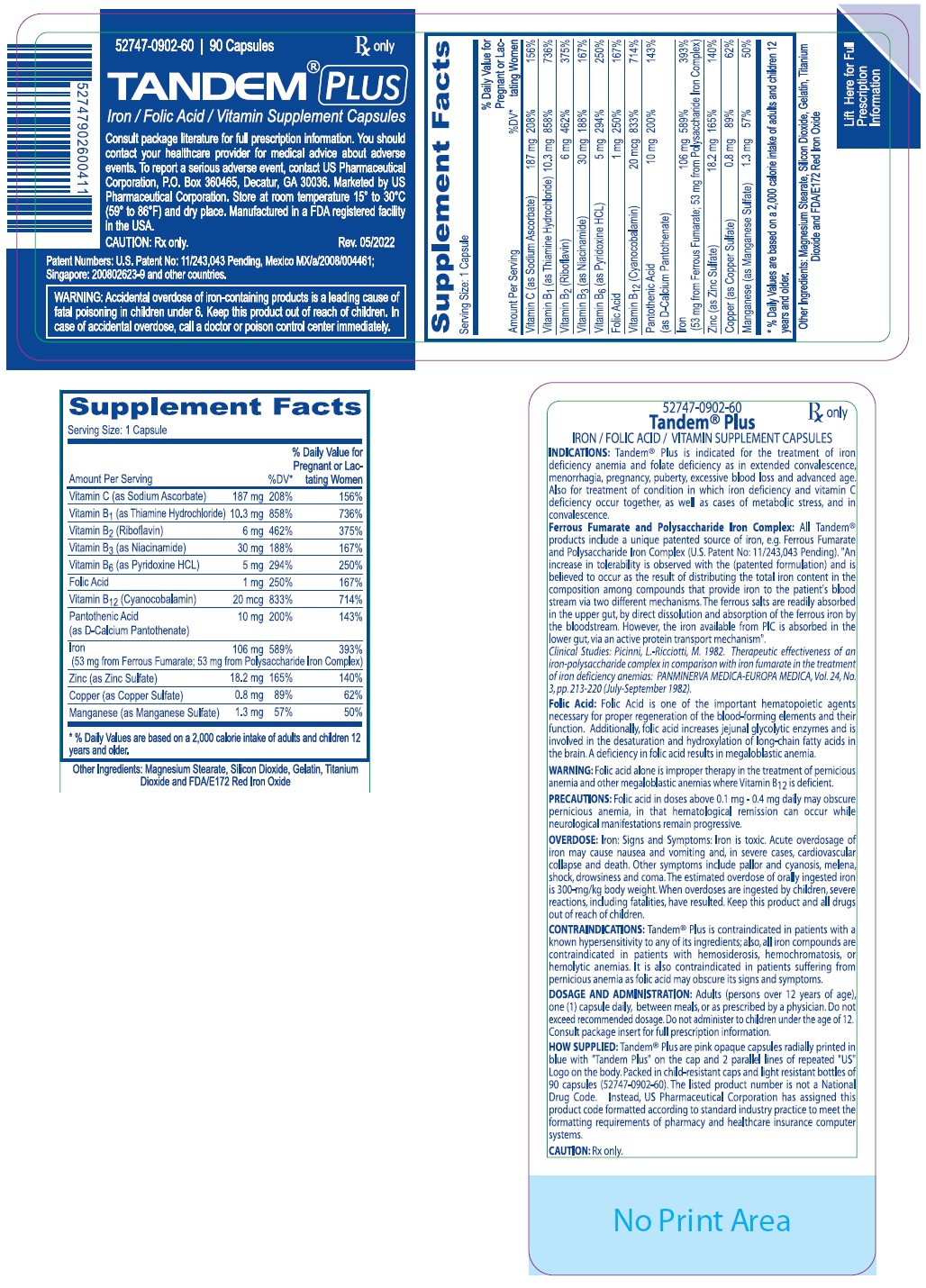 DRUG LABEL: TANDEM PLUS
NDC: 52747-902 | Form: CAPSULE
Manufacturer: U.S. Pharmaceutical Corporation
Category: other | Type: DIETARY SUPPLEMENT
Date: 20220606

ACTIVE INGREDIENTS: SODIUM ASCORBATE 187 mg/1 1; THIAMINE HYDROCHLORIDE 10.3 mg/1 1; RIBOFLAVIN 6 mg/1 1; NIACINAMIDE 30 mg/1 1; PYRIDOXINE HYDROCHLORIDE 5 mg/1 1; FOLIC ACID 1 mg/1 1; CYANOCOBALAMIN 20 ug/1 1; CALCIUM PANTOTHENATE 10 mg/1 1; FERROUS FUMARATE 53 mg/1 1; IRON POLYMALTOSE 53 mg/1 1; ZINC SULFATE MONOHYDRATE 18.2 mg/1 1; CUPRIC SULFATE 0.8 mg/1 1; MANGANESE SULFATE 1.3 mg/1 1
INACTIVE INGREDIENTS: MAGNESIUM STEARATE; SILICON DIOXIDE; GELATIN, UNSPECIFIED; TITANIUM DIOXIDE; FERRIC OXIDE RED

TANDEM® PLUS

STATEMENT OF IDENTITY

Supplement Facts
Serving Size: 1 Capsule
Amount Per Serving |  | %DV* | % Daily Value for; Pregnant or; Lactating Women
Vitamin C (as Sodium Ascorbate) | 187 mg | 208% | 156%
Vitamin B1 (as Thiamine Hydrochloride) | 10.3 mg | 858% | 736%
Vitamin B2 (Riboflavin) | 6 mg | 462% | 375%
Vitamin B3 (as Niacinamide) | 30 mg | 188% | 167%
Vitamin B6 (as Pyridoxine HCL) | 5 mg | 294% | 250%
Folic Acid | 1 mg | 250% | 167%
Vitamin B12 (Cyanocobalamin) | 20 mcg | 833% | 714%
Pantothenic Acid | 10 mg | 200% | 143%
(as D-Calcium Pantothenate)
Iron | 106 mg | 589% | 393%
(53 mg from Ferrous Fumarate; 53 mg from Polysaccharide Iron
Complex)
Zinc (as Zinc Sulfate) | 18.2 mg | 165% | 140%
Copper (as Copper Sulfate) | 0.8 mg | 89% | 62%
Manganese (as Manganese Sulfate) | 1.3 mg | 57% | 50%
* % Daily Values are based on a 2,000 calorie intake of adults and children 12 years and older.

Other Ingredients: Magnesium Stearate, Silicon Dioxide, Gelatin, Titanium Dioxide and FDA/E172 Red Iron Oxide

Tandem® Plus

IRON / FOLIC ACID / VITAMIN SUPPLEMENT CAPSULES

INDICATIONS: Tandem® Plus is an Rx dietary supplement indicated for the treatment of iron deficiency anemia and folate deficiency as in extended convalescence, menorrhagia, pregnancy, puberty, excessive blood loss and advanced age. It is also for treatment of condition in which iron deficiency and vitamin C deficiency occur together, as well as cases of metabolic stress, and in convalescence.

Ferrous Fumarate and Polysaccharide Iron Complex: All Tandem® products include a unique patented source of iron, e.g. Ferrous Fumarate and Polysaccharide Iron Complex (U.S. Patent No: 11/243,043 Pending). "An increase in tolerability is observed with the (patented formulation) and is believed to occur as the result of distributing the total iron content in the composition among compounds that provide iron to the patient's blood stream via two different mechanisms. The ferrous salts are readily absorbed in the upper gut, by direct dissolution and absorption of the ferrous iron by the bloodstream. However, the iron available from PIC is absorbed in the lower gut, via an active protein transport mechanism".

Clinical Studies: Picinni, L.-Ricciotti, M. 1982. Therapeutic effectiveness of an iron-polysaccharide complex in comparison with iron fumarate in the treatment of iron deficiency anemias: PANMINERVA MEDICA-EUROPA MEDICA, Vol. 24, No. 3, pp. 213-220 (July-September 1982).

Folic Acid: Folic Acid is one of the important hematopoietic agents necessary for proper regeneration of the blood-forming elements and their function. Additionally, folic acid increases jejunal glycolytic enzymes and is involved in the desaturation and hydroxylation of long-chain fatty acids in the brain. A deficiency in folic acid results in megaloblastic anemia.

WARNINGS

WARNING: Folic acid alone is improper therapy in the treatment of pernicious anemia and other megaloblastic anemias where Vitamin B12 is deficient.

PRECAUTIONS

PRECAUTIONS: Folic acid alone in doses above 0.1 mg - 0.4 mg daily may obscure pernicious anemia, in that hematological remission can occur while neurological manifestations remain progressive.

DOSAGE AND ADMINISTRATION

OVERDOSE: Iron: Signs and Symptoms: Iron is toxic. Acute overdosage of iron may cause nausea and vomiting and, in severe cases, cardiovascular collapse and death. Other symptoms include pallor and cyanosis, melena, shock, drowsiness and coma. The estimated overdose of orally ingested iron is 300-mg/kg body weight. When overdoses are ingested by children, severe reactions, including fatalities, have resulted. Keep this product and all drugs out of reach of children.

CONTRAINDICATIONS: Tandem® Plus is contraindicated in patients with a known hypersensitivity to any of its ingredients; also, all iron compounds are contraindicated in patients with hemosiderosis, hemochromatosis, or hemolytic anemias. It is also contraindicated in patients suffering from pernicious anemia as folic acid may obscure its signs and symptoms.

DOSAGE AND ADMINISTRATION: Adults (persons over 12 years of age), one (1) capsule daily, between meals, or as prescribed by a physician. Do not exceed recommended dosage. Do not administer to children under the age of 12. Consult package insert for full prescription information.

SAFE HANDLING WARNING

HOW SUPPLIED: Tandem® Plus are pink opaque capsules radially printed in blue with "Tandem Plus" on the cap and 2 parallel lines of repeated "US" Logo on the body. Packed in child-resistant caps and light resistant bottles of 90 capsules (52747-0902-60). The listed product number is not a National Drug Code. Instead, US Pharmaceutical Corporation has assigned this product code formatted according to standard industry practice to meet the formatting requirements of pharmacy and healthcare insurance computer systems.

HEALTH CLAIM

CAUTION: Rx only.

Consult package literature for full prescription information. You should contact your healthcare provider for medical advice about adverse events. To report a serious adverse event, contact US Pharmaceutical Corporation, P.O. Box 360465, Decatur, GA 30036. Marketed by US Pharmaceutical Corporation. Store at room temperature 15° to 30°C (59° to 86°F) and dry place. Manufactured in a FDA registered facility in the USA.

Rev. 05/2022

Patent Numbers: U.S. Patent No: 11/243,043 Pending, Mexico MX/a/2008/004461; Singapore: 200802623-9 and other countries.

WARNING: Accidental overdose of iron-containing products is a leading cause of fatal poisoning in children under 6. Keep this product out of reach of children. In case of accidental overdose, call a doctor or poison control center immediately.